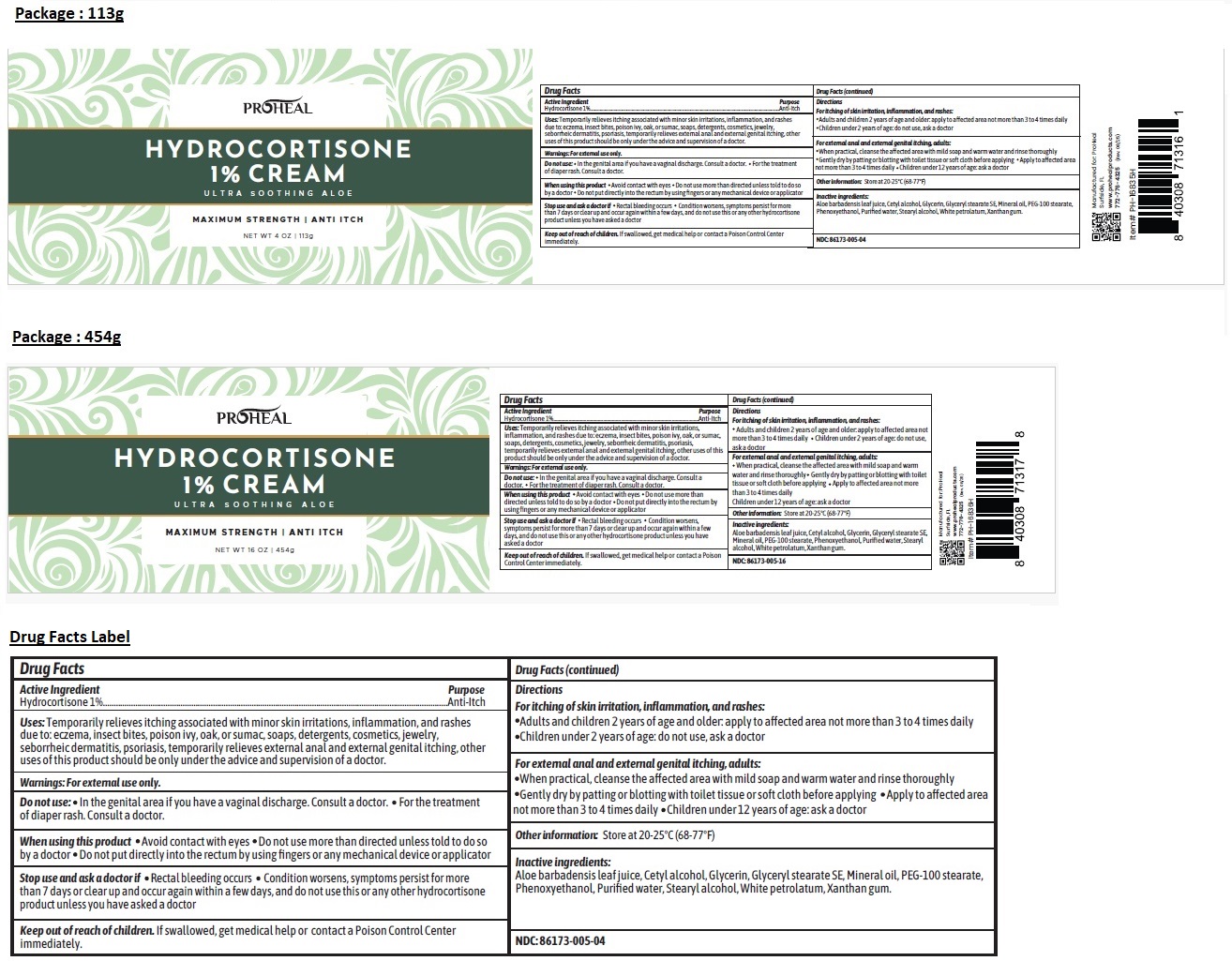 DRUG LABEL: PROHEAL HYDROCORTISONE 1% MAXIMUM STRENGTH PLUS ALOE
NDC: 86173-005 | Form: CREAM
Manufacturer: Click Industries LLC
Category: otc | Type: HUMAN OTC DRUG LABEL
Date: 20250825

ACTIVE INGREDIENTS: HYDROCORTISONE 1 g/100 g
INACTIVE INGREDIENTS: ALOE VERA LEAF JUICE; CETYL ALCOHOL; GLYCERIN; GLYCERYL STEARATE SE; MINERAL OIL; PEG-100 MONOSTEARATE; PHENOXYETHANOL; WATER; STEARYL ALCOHOL; WHITE PETROLATUM; XANTHAN GUM

PROHEAL HYDROCORTISONE 1% CREAM ULTRA SOOTHING ALOE

Active Ingredient

Hydrocortisone 1%

Purpose

Anti-Itch

Uses:

Temporarily relieves itching associated with minor skin irritations, inflammation, and rashes due to: eczema, insect bites, poison ivy, oak, or sumac, soaps, detergents, cosmetics, jewelry, seborrheic dermatitis, psoriasis, temporarily relieves external anal and external genital itching, other uses of this product should be only under the advice and supervision of a doctor.

Warnings:

For external use only.

Do not use: • In the genital area if you have a vaginal discharge. Consult a doctor. • For the treatment of diaper rash. Consult a doctor.

When using this product • Avoid contact with eyes • Do not use more than directed unless told to do so by a doctor • Do not put directly into the rectum by using fingers or any mechanical device or applicator

Stop use and ask a doctor if • Rectal bleeding occurs • Condition worsens, symptoms persist for more than 7 days or clear up and occur again within a few days, and do not use this or any other hydrocortisone product unless you have asked a doctor

Keep out of reach of children. If swallowed, get medical help or contact a Poison Control Center immediately.

Directions

For itching of skin irritation, inflammation, and rashes:
• Adults and children 2 years of age and older: apply to affected area not more than 3 to 4 times daily • Children under 2 years of age: do not use, ask a doctor

For external anal and external genital itching, adults:
• When practical, cleanse the affected area with mild soap and warm water and rinse thoroughly • Gently dry by patting or blotting with toilet tissue or soft cloth before applying • Apply to affected area not more than 3 to 4 times daily • Children under 12 years of age: ask a doctor

Other information:

Store at 20-25°C (68-77°F)

Inactive ingredients:

Aloe barbadensis leaf juice, Cetyl alcohol, Glycerin, Glyceryl stearate SE, Mineral oil, PEG-100 stearate, Phenoxyethanol, Purified water, Stearyl alcohol, White petrolatum, Xanthan gum.

ULTRA SOOTHING ALOE

Manufactured for: ProHeal
Surfside, FL

www.prohealproducts.com
772-776-4325 (Rev. 08/25)